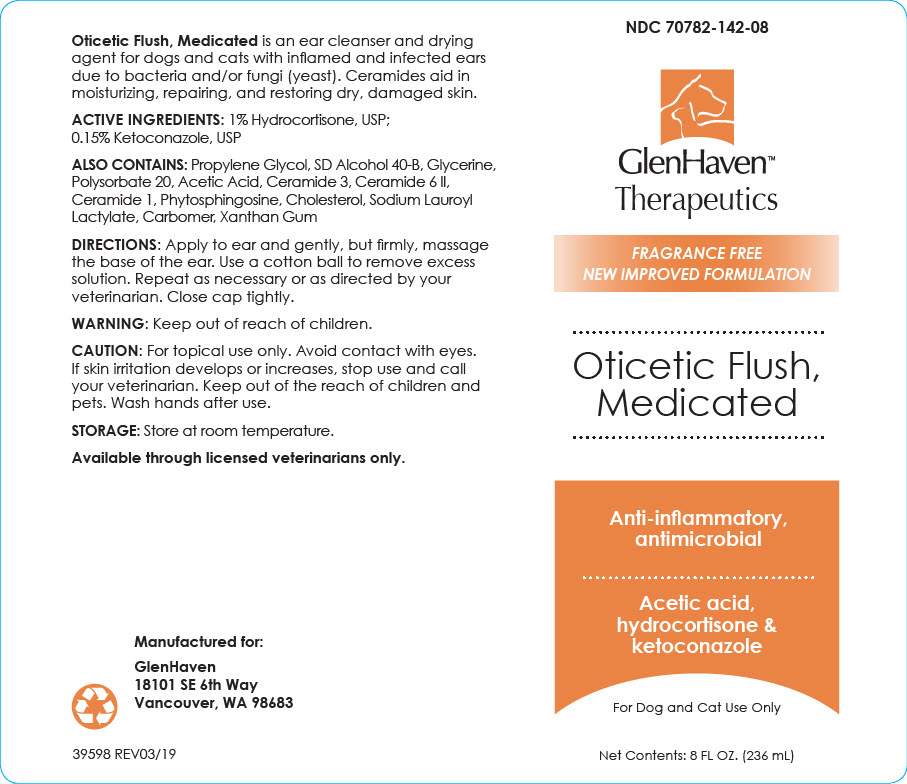 DRUG LABEL: Oticetic Flush, Medicated
NDC: 70782-142 | Form: SOLUTION
Manufacturer: GlenHaven LLC
Category: animal | Type: OTC ANIMAL DRUG LABEL
Date: 20211208

ACTIVE INGREDIENTS: Hydrocortisone 10 mg/1 mL; Ketoconazole 1.5 mg/1 mL

Oticetic Flush, Medicated

VETERINARY INDICATIONS

Oticetic Flush, Medicated is an ear cleanser and drying agent for dogs and cats with inflamed and infected ears due to bacteria and/or fungi (yeast). Ceramides aid in moisturizing, repairing, and restoring dry, damaged skin.

DESCRIPTION

ACTIVE INGREDIENTS: 1% Hydrocortisone, USP; 0.15% Ketoconazole, USP

ALSO CONTAINS: Propylene Glycol, SD Alcohol 40-B, Glycerine, Polysorbate 20, Acetic Acid, Ceramide 3, Ceramide 6 II, Ceramide 1, Phytosphingosine, Cholesterol, Sodium Lauroyl Lactylate, Carbomer, Xanthan Gum

DOSAGE AND ADMINISTRATION

DIRECTIONS: Apply to ear and gently, but firmly, massage the base of the ear. Use a cotton ball to remove excess solution. Repeat as necessary or as directed by your veterinarian. Close cap tightly.

WARNINGS

WARNING: Keep out of reach of children.

CAUTION: For topical use only. Avoid contact with eyes. If skin irritation develops or increases, stop use and call your veterinarian. Keep out of the reach of children and pets. Wash hands after use.

HOW SUPPLIED

STORAGE: Store at room temperature.

Available through licensed veterinarians only.

Manufactured for:
GlenHaven
18101 SE 6th Way
Vancouver, WA 98683

39598 REV03/19

PRINCIPAL DISPLAY PANEL - 236 mL Bottle Label

NDC 70782-142-08

GlenHaven™
Therapeutics

FRAGRANCE FREE
NEW IMPROVED FORMULATION

Oticetic Flush,
Medicated

Anti-inflammatory,
antimicrobial

Acetic acid,
hydrocortisone &
ketoconazole

For Dog and Cat Use Only

Net Contents: 8 FL OZ. (236 mL)